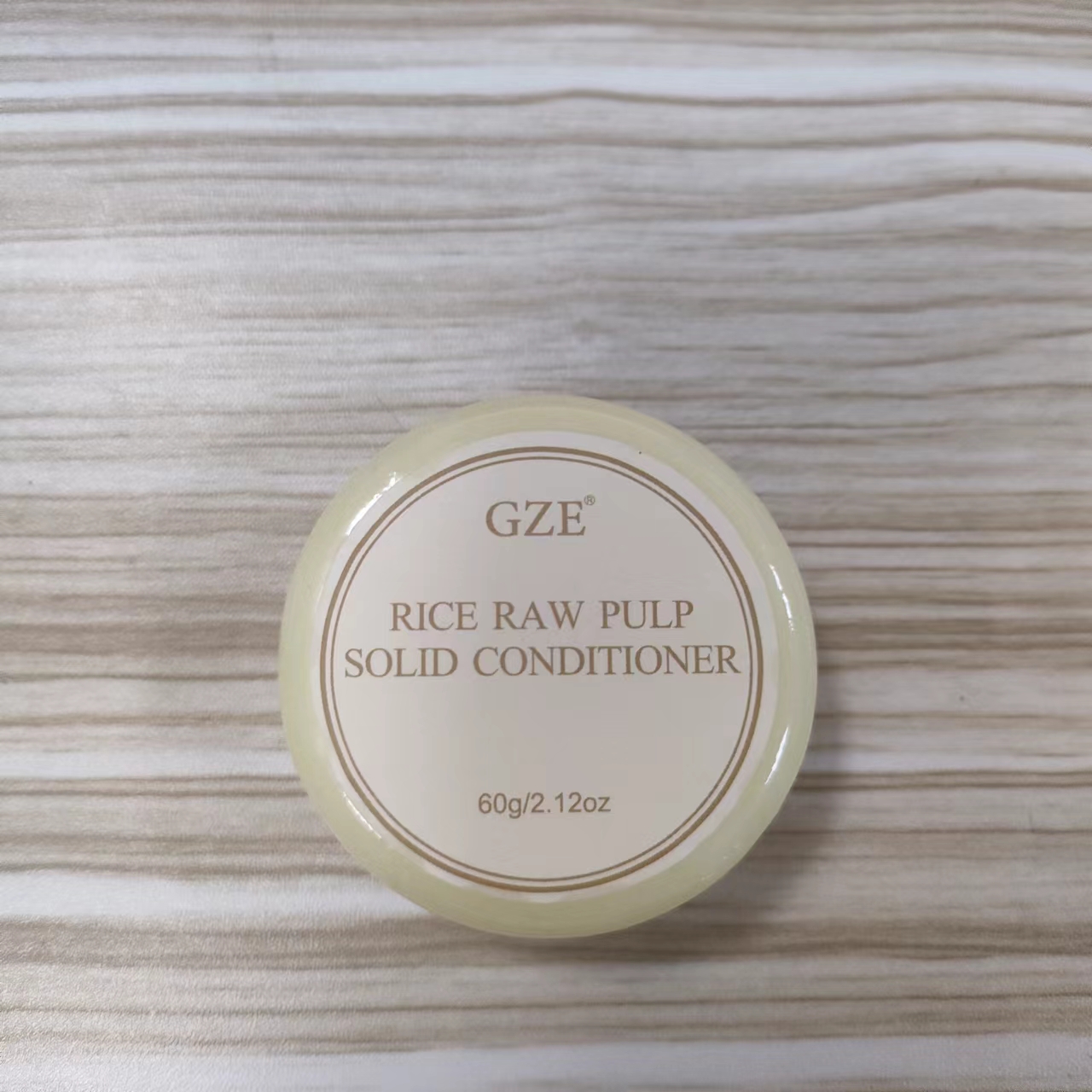 DRUG LABEL: GZE RICE RAW PULP SOLID CONDITIONER
NDC: 74458-110 | Form: SOAP
Manufacturer: Guangzhou Yilong Cosmetics Co., Ltd
Category: otc | Type: HUMAN OTC DRUG LABEL
Date: 20241026

ACTIVE INGREDIENTS: SIMMONDSIA CHINENSIS (JOJOBA) SEED OIL 10 g/100 g; COCOS NUCIFERA (COCONUT) OIL 10 g/100 g
INACTIVE INGREDIENTS: BUTYROSPERMUM PARKII (SHEA) BUTTER; BAMBUSA VULGARIS LEAF; RICE BRAN OIL; ORYZA SATIVA (RICE) BRAN

GZE RICE RAW PULP SOLID CONDITIONER

ACTIVE INGREDIENT

Simmondsia Chinensis (Jojoba) Seed Oil

Cocos Nucifera (Coconut) Oil

INACTIVE INGREDIENT

Oryza Sativa (Rice) Bran Oil

Oryza Sativa (Rice) Extract

Bambusa Vulgaris Leaf Extract

Butyrospermum Parkii (Shea) Butter

PURPOSE

Hair and sclap care.

INDICATIONS AND USAGE

After shampooing, while water runs over hair, slide conditioner bar over hairto activate, work into the ends then rinse. For deeper conditioning, repeat.

WARNINGS

For external use only.

Stop use and ask a doctor if rash occurs.

Do not use on damaged or broken skin.

When using this product keep out of eyes. Rinse with water to remove.

Keep out of reach of children. If swallowed, get medical help or contact a Poison Control Center right away.

DOSAGE AND ADMINISTRATION

After shampooing, while water runs over hair, slide conditioner bar over hairto activate, work into the ends then rinse. For deeper conditioning, repeat.